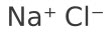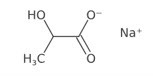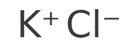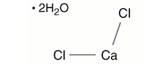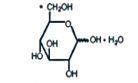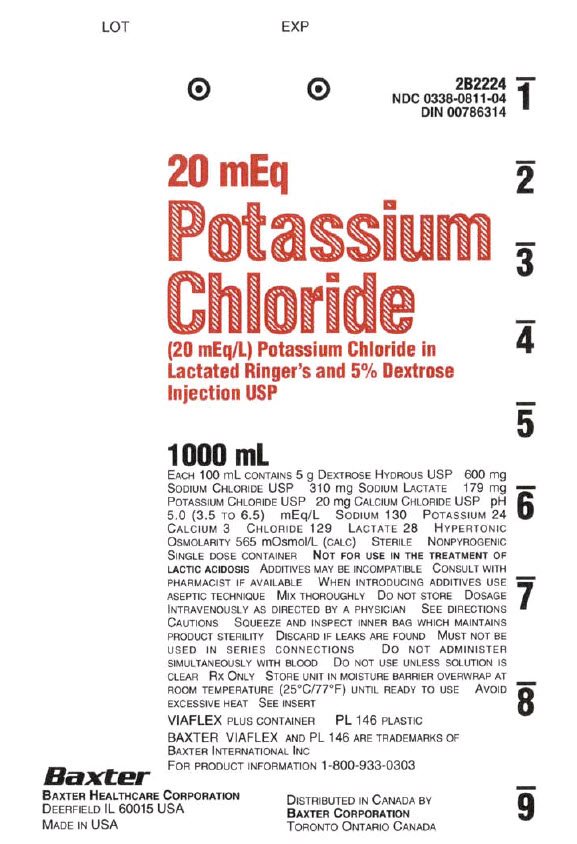 DRUG LABEL: Potassium Chloride in Lactated Ringers and Dextrose
NDC: 0338-0811 | Form: INJECTION, SOLUTION
Manufacturer: Baxter Healthcare Corporation
Category: prescription | Type: HUMAN PRESCRIPTION DRUG LABEL
Date: 20251029

ACTIVE INGREDIENTS: DEXTROSE MONOHYDRATE 5 g/100 mL; SODIUM CHLORIDE 600 mg/100 mL; SODIUM LACTATE 310 mg/100 mL; POTASSIUM CHLORIDE 179 mg/100 mL; CALCIUM CHLORIDE 20 mg/100 mL
INACTIVE INGREDIENTS: WATER

HIGHLIGHTS OF PRESCRIBING INFORMATION

These highlights do not include all the information needed to use POTASSIUM CHLORIDE IN LACTATED RINGER’S AND DEXTROSE (5%) INJECTION safely and effectively. See full prescribing information for POTASSIUM CHLORIDE IN LACTATED RINGER’S AND DEXTROSE (5%) INJECTION.
POTASSIUM CHLORIDE IN LACTATED RINGER’S AND DEXTROSE injection, for intravenous use
Initial U.S. Approval: 1985

RECENT MAJOR CHANGES

Dosage and Administration (2.1, 2.2, 2.3, 2.4) 10/2025
Contraindications (4) 10/2025
Warnings and Precautions (5.1, 5.2, 5.3, 5.4, 5.5, 5.6, 5.7, 5.8, 5.9, 5.10, 5.11) 10/2025

1 INDICATIONS AND USAGE

Potassium Chloride in Lactated Ringer’s and Dextrose (5%) Injection is indicated for use as a source of water, electrolytes, and calories or as an alkalinizing agent in adults and pediatric patients. (1)

2 DOSAGE AND ADMINISTRATION

- The recommended dosage and duration are based on the patient’s age, weight, clinical condition, and concomitant therapy. (2.1)
- To reduce the risk of air embolism, adhere to the preparation instructions. (2.2, 5.2)
- Potassium Chloride in Lactated Ringer’s and Dextrose (5%) Injection is for intravenous use. (2.3)
- Use a peripheral vein to administer if the final dextrose concentration is 5% or less, and the osmolarity is less than 900 mOsm/L. (2.3).
- Consider using a central vein to administer hypertonic solutions with osmolarity of 900 mOsm/L or more to avoid venous irritation, including phlebitis. (2.3)
- Do not administer Potassium Chloride in Lactated Ringer’s and Dextrose (5%) Injection simultaneously with ceftriaxone in neonates (28 days of age or younger) due to serious risks. (2.4)
- See full prescribing information for information dosage considerations, preparation, administration, and drug incompatibilities. (2)

3 DOSAGE FORMS AND STRENGTHS

Injection: Potassium Chloride (20 mEq) in Lactated Ringer’s and Dextrose (5%) Injection, USP packaged in a single-dose VIAFLEX plastic container: 1000 mL. (3)

4 CONTRAINDICATIONS

- Concomitant treatment with ceftriaxone in neonates (28 days of age or younger). (4)
- Patients with known hypersensitivity to any of the components of Potassium Chloride in Lactated Ringer’s solution and Dextrose (5%) Injection (4)
- Patients with clinically significant hyperkalemia (4).
- Patients with clinically significant hyperglycemia (4).

5 WARNINGS AND PRECAUTIONS

- Serious Risks with Inappropriate Use with Ceftriaxone: Deaths have occurred in neonates (28 days of age or younger) who received concomitant intravenous calcium-containing solutions with ceftriaxone. In patients older than 28 days, ceftriaxone and Potassium Chloride in Lactated Ringer’s and Dextrose (5%) Injection may be administered sequentially if the infusion lines are thoroughly flushed between infusions. (4, 5.1, 8.4)
- Air Embolism: Use a non-vented infusion set or close the vent on a vented set and use a dedicated line without any connections. Pressure infusion is not recommended to increase flow rates, but if necessary, remove all air from the bag prior to initiating infusion. (5.2)
- Hypersensitivity Reactions: Stop the Potassium Chloride in Lactated Ringer’s and Dextrose (5%) Injection infusion immediately if signs or symptoms of a hypersensitivity reaction develop. (5.3)
- Potassium Imbalances, Hyponatremia, Neonatal Hypoglycemia, Hyperglycemia and Hyperosmolar Hyperglycemic State, Hypercalcemia, Fluid Overload, Acid-Base Imbalances, Interference with Interpretation of Serum Lactate Levels in Patients with Severe Metabolic Acidosis: See Full Prescribing Information for risk management recommendations. (5.4, 5.5, 5.6, 5.7, 5.8, 5.9, 5.10, 5.11)

6 ADVERSE REACTIONS

Common adverse reactions include infusion site reactions and symptoms of hypersensitivity reactions (e.g., pruritus, dyspnea, urticaria, rash, cough). (6)

To report SUSPECTED ADVERSE REACTIONS, contact Baxter Healthcare at 1-866-888-2472 or FDA at 1-800-FDA-1088 or www.fda.gov/medwatch.

7 DRUG INTERACTIONS

- Drugs that Affect Electrolyte and/or Fluid Balance: Avoid concomitant use. If concomitant use cannot be avoided, closely monitor electrolyte concentrations and fluid balance. (7.1)
- Lithium: Avoid concomitant use. If concomitant use is unavoidable, monitor serum lithium concentrations more frequently. (7.2)
- Digoxin: Consider reducing the volume or rate of Potassium Chloride in Lactated Ringer’s and Dextrose (5%) Injection due to the increased risk of digoxin toxicity with calcium-containing solutions. (7.3)
- Drugs with pH-Dependent Renal Elimination: Renal clearance of acidic drugs may be increased. In contrast, renal clearance of alkaline drugs may be decreased. (7.4)

8 USE IN SPECIFIC POPULATIONS

- Closely monitor plasma electrolyte concentrations in young pediatric patients with immature kidney function. (8.4)
- Neonates are at increased risk of developing hypo- or hyperglycemia. Closely monitor to ensure adequate glycemic control. (8.4)
- Geriatric patients are more likely to have decreased renal function. Consider monitoring renal function and starting the infusion at the low end of the dosing range. (8.5)
- Avoid in patients with severe renal impairment. (8.6)
- Patients with severe hepatic impairment may have impaired lactate metabolism. Closely monitor serum lactate levels and acid-base status. (8.7)

FULL PRESCRIBING INFORMATION

1 INDICATIONS AND USAGE

Potassium Chloride in Lactated Ringer’s and Dextrose (5%) Injection is indicated for use as a source of water, electrolytes, and calories or as an alkalinizing agent in adults and pediatric patients.

2 DOSAGE AND ADMINISTRATION

2.1 Dosage Considerations

The recommended dosage and duration of Potassium Chloride in Lactated Ringer’s and Dextrose (5%) Injection is based on the patient’s age, weight, clinical condition, and concomitant therapy. Evaluate the patient’s clinical status and monitor changes in blood glucose and electrolyte concentrations especially during prolonged use of Potassium Chloride in Lactated Ringer’s and Dextrose (5%) Injection to optimize clinical status.

2.2 Important Preparation Instructions

Visually inspect the Potassium Chloride in Lactated Ringer’s and Dextrose (5%) Injection solution for particulate matter and discoloration. Do not administer Potassium Chloride in Lactated Ringer’s and Dextrose (5%) Injection unless the solution is clear and the container seals are intact.

If additives are determined to be compatible with Potassium Chloride in Lactated Ringer’s and Dextrose (5%) Injection then using aseptic technique, mix thoroughly; do not store solutions containing additives. After mixing, do not use if there is discoloration or formation of precipitates.

To reduce the risk of air embolism, adhere to the following preparation instructions for Potassium Chloride in Lactated Ringer’s and Dextrose (5%) Injection [see Warnings and Precautions (5.2)]:

- Use a non-vented infusion set or close the vent on a vented set.
- Use a dedicated line without any connections (do not connect flexible containers in series).
- The use of pressure infusion is not recommended as a method to increase flow rates. However, if pressure infusion is required, ensure that any air within the bag is fully evacuated prior to initiation of infusion.
- If using a pumping device to administer Potassium Chloride in Lactated Ringer’s and Dextrose (5%) Injection, turn off the pump before the container is empty.

Preparation Instructions

1. Tear overwrap downside at slit and remove solution container.
2. Visually inspect the container.
  1. If the outlet port protector is damaged, detached, or not present, discard container as solution path sterility may be impaired.
  2. Some opacity of the plastic due to moisture absorption during the sterilization process may be observed. This is normal and does not affect the solution quality or safety. The opacity will diminish gradually.
3. Check for minute leaks by squeezing inner bag firmly. If leaks are found, discard solution as sterility may be impaired.
4. If supplemental medication is desired, follow directions below [see Dosage and Administration (2.3)].

Preparation for Administration

1. Suspend container from eyelet support.
2. Remove protector from outlet port at bottom of container.
3. Attach administration set according to its accompanying directions.

2.3 Important Administration Instructions

Potassium Chloride in Lactated Ringer’s and Dextrose (5%) Injection is for intravenous use.

Use immediately after removing the overwrap. Discard the unused portion.

- Use a peripheral vein to administer Potassium Chloride in Lactated Ringer’s and Dextrose (5%) Injection if the final dextrose concentration is 5% or less, and the osmolarity is less than 900 mOsm/L.
- Consider using a central vein to administer hypertonic solutions with osmolarity of 900 mOsm/L or more to avoid venous irritation [see Warnings and Precautions (5.7)].

Some additives may be incompatible [see Dosage and Administration (2.4) and Contraindications (4)].

To Add Medication Before Solution Administration

1. Prepare medication site.
2. Using syringe with 19 to 22 gauge needle, puncture resealable medication port and inject.
3. Mix solution and medication thoroughly. For high density medication such as potassium chloride, squeeze ports while ports are upright and mix thoroughly.

To Add Medication During Solution Administration

1. Close clamp on the set.
2. Prepare medication site.
3. Using syringe with19 to 22 gauge needle, puncture resealable medication port and inject.
4. Remove container from IV pole and/or turn to an upright position.
5. Evacuate both ports by squeezing them while container is in the upright position.
6. Mix solution and medication thoroughly.
7. Return container to in use position and continue administration.

2.4 Drug Incompatibilities

Do not administer Potassium Chloride in Lactated Ringer’s and Dextrose (5%) Injection simultaneously with ceftriaxone in neonates (28 days of age or younger) due to serious risks [see Contraindications (4) and Warnings and Precautions (5.1)]. However, in patients older than 28 days, ceftriaxone and Potassium Chloride in Lactated Ringer’s and Dextrose (5%) Injection may be administered sequentially if the infusion lines are thoroughly flushed between infusions with a compatible fluid [see Warnings and Precautions (5.1)].

Do not administer Potassium Chloride in Lactated Ringer’s and Dextrose (5%) Injection simultaneously with citrate anticoagulated/preserved blood through the same administration set because of the likelihood of coagulation precipitated by the calcium content of Potassium Chloride in Lactated Ringer’s and Dextrose (5%) Injection.

3 DOSAGE FORMS AND STRENGTHS

Injection: Potassium Chloride (20 mEq) in Lactated Ringer’s and Dextrose (5%) Injection, USP as a clear, sterile, and nonpyrogenic solution packaged in a single-dose VIAFLEX plastic container: 1,000 mL.

4 CONTRAINDICATIONS

Potassium Chloride in Lactated Ringer’s and Dextrose (5%) Injection is contraindicated in:

- Neonates (28 days of age or younger) who are receiving concomitant treatment with ceftriaxone, even if separate infusion lines are used, due to the risk of fatal ceftriaxone-calcium salt precipitation in the neonate’s bloodstream [see Warnings and Precautions (5.1) and Specific Populations (8.4)].
- Patients with known hypersensitivity to any of the components of Potassium Chloride in Lactated Ringer’s solution and Dextrose (5%) Injection [see Warnings and Precautions (5.3)].
- Patients with clinically significant hyperkalemia [see Warnings and Precautions (5.4)].
- Patients with clinically significant hyperglycemia [see Warnings and Precautions (5.7)].

5 WARNINGS AND PRECAUTIONS

5.1 Serious Risk with Concomitant Use with Ceftriaxone

Precipitation of ceftriaxone-calcium can occur when ceftriaxone is mixed with calcium-containing solutions, such as Potassium Chloride in Lactated Ringer’s and Dextrose (5%) Injection, in the same intravenous administration line. Deaths have occurred in neonates (28 days of age or younger) who received concomitant intravenous calcium-containing solutions with ceftriaxone resulting from calcium-ceftriaxone precipitates in the lungs and kidneys, even when separate infusion lines were used.

Potassium Chloride in Lactated Ringer’s and Dextrose (5%) Injection is contraindicated in neonates who receive ceftriaxone [see Contraindications (4), Use in Specific Populations (8.4)]. However, in patients older than 28 days, ceftriaxone and Potassium Chloride in Lactated Ringer’s and Dextrose (5%) Injection may be administered sequentially if the infusion lines are thoroughly flushed between infusions with a compatible fluid.

5.2 Air Embolism

Cases of air embolism have been reported with pressurized administration of intravenous fluids. Air embolism may result in stroke, organ ischemia and/or infarction, and death.

Use a non-vented infusion set or close the vent on a vented set and use a dedicated line without any connections.

If administration is controlled by a pumping device, care must be taken to discontinue the pumping action before the container is empty.

If administration is controlled by a pumping device, care must be taken to discontinue the pumping action before the container is empty.

Pressure infusion is not recommended to increase flow rates, but if necessary, ensure all air is removed from the bag before infusion.

Refrain from applying excessive pressure (>300mmHg) causing distortion to the container such as wringing or twisting. Such handling could result in breakage of the container [see Dosage and Administration (2.2)].

5.3 Hypersensitivity Reactions

Hypersensitivity reactions, including anaphylaxis and angioedema, have been reported with Lactated Ringer’s solution. Stop the Potassium Chloride in Lactated Ringer’s and Dextrose (5%) Injection infusion immediately and treat patient accordingly if signs or symptoms of a hypersensitivity reaction develop. Initiate appropriate treatment as clinically indicated.

5.4 Potassium Imbalances

Hyperkalemia
Potassium-containing solutions, including Potassium Chloride in Lactated Ringer’s and Dextrose (5%) Injection, may increase the risk of hyperkalemia. This risk is increased in patients predisposed to hyperkalemia including those with severe renal impairment, acute dehydration, extensive tissue injury or burns, heart failure, or in those using concomitant drugs that are associated with hyperkalemia.

Avoid use of Potassium Chloride in Lactated Ringer’s and Dextrose (5%) Injection in patients with, or at increased risk for, hyperkalemia. If use cannot be avoided in these patients, closely monitor serum potassium concentrations.

5.5 Hyponatremia

Potassium Chloride in Lactated Ringer’s and Dextrose (5%) Injection may cause hyponatremia. Hyponatremia can lead to acute hyponatremic encephalopathy characterized by headache, nausea, seizures, lethargy and vomiting. The risk of hospital-acquired hyponatremia is increased in younger pediatric patients, geriatric patients, patients treated with diuretics, patients with cardiac or pulmonary failure, or patients with the syndrome of inappropriate antidiuretic hormone (SIADH) (e.g., postoperative patients, patients concomitantly treated with arginine vasopressin analogs, or certain antiepileptic, psychotropic, or cytotoxic drugs) [see Drug Interactions (7.1), Use in Specific Populations (8.4)]. Avoid Potassium Chloride in Lactated Ringer’s and Dextrose (5%) Injection in patients with or at risk for hyponatremia. If use cannot be avoided in these patients, closely monitor serum sodium concentrations.

Rapid correction of hyponatremia may result in serious neurologic complications such as osmotic demyelination syndrome (ODS). To avoid complications, monitor serum sodium and chloride concentrations, fluid status, acid-base balance, and neurologic status.

5.6 Neonatal Hypoglycemia

Neonates, especially preterm neonates with low birth weight, are at increased risk of developing hypoglycemia. Closely monitor blood glucose concentration during treatment with intravenous dextrose solutions to ensure adequate glycemic control in order to avoid potential long-term adverse effects.

5.7 Hyperglycemia and Hyperosmolar Hyperglycemic State

Administration of solutions containing dextrose and lactate in patients with impaired glucose tolerance including those with diabetes mellitus may worsen hyperglycemia. Hyperglycemia is associated with an increase in serum osmolality, which can result in hypovolemia and electrolyte imbalances due to osmotic diuresis.

Patients with underlying central nervous system disease or renal impairment who receive dextrose infusions may be at greater risk of developing hyperosmolar hyperglycemic state.

While using Potassium Chloride in Lactated Ringer’s and Dextrose (5%) Injection, closely monitor blood glucose concentrations and treat hyperglycemia to maintain glucose concentrations within normal limits. Anti-diabetic drugs may need to be started or dosages of these drugs may need to be increased to maintain optimal blood glucose concentrations.

5.8 Hypercalcemia

Potassium Chloride in Lactated Ringer’s and Dextrose (5%) Injection contains calcium salts and may cause hypercalcemia. Avoid administration of Potassium Chloride in Lactated Ringer’s and Dextrose (5%) Injection in patients with hypercalcemia, those with calcium-containing renal calculi or history of such calculi, those with conditions predisposing to hypercalcemia, or those treated with concomitant thiazide diuretics or vitamin D.

5.9 Fluid Overload

Depending on the administered volume and the infusion rate, administration of Potassium Chloride in Lactated Ringer’s and Dextrose (5%) Injection can cause fluid overload, including pulmonary edema.

Avoid Potassium Chloride in Lactated Ringer’s and Dextrose (5%) Injection in patients at risk for fluid and/or solute overload including patients with severe renal impairment. If use cannot be avoided in these patients, monitor fluid balance, electrolyte concentrations and acid base balance, especially during prolonged use.

5.10 Acid/Base Imbalances

Because lactate is metabolized to bicarbonate, administration of Potassium Chloride in Lactated Ringer’s and Dextrose (5%) Injection may result in, or worsen, metabolic alkalosis. Closely monitor the acid-base balance in patients with, or at risk of, alkalosis.

In patients with severe hepatic impairment, decreased lactate metabolism may result in worsening anion gap metabolic acidosis. Avoid Potassium Chloride in Lactated Ringer’s and Dextrose (5%) Injection in patients with severe hepatic impairment. If use cannot be avoided in these patients, closely monitor serum bicarbonate levels.

5.11 Interference of Potassium Chloride in Lactated Ringer’s and Dextrose (5%) Injection with Interpretation of Serum Lactate Levels in Patients with Severe Metabolic Acidosis

Administration of Potassium Chloride in Lactated Ringer’s and Dextrose (5%) Injection may result in interference with the interpretation of serum lactate levels in patients with severe metabolic acidosis, including lactic acidosis [see Drug Interactions (7.5)].

6 ADVERSE REACTIONS

The following serious adverse reactions are discussed in greater detail in other sections of the labeling:

- Serious Risk with Concomitant Use with Ceftriaxone [see Warnings and Precautions (5.1)]
- Air Embolism [see Warnings and Precautions (5.2)]
- Hypersensitivity Reactions [see Warnings and Precautions (5.3)]
- Potassium Imbalances [see Warnings and Precautions (5.4)]
- Hyponatremia [see Warnings and Precautions (5.5)]
- Neonatal Hypoglycemia [see Warnings and Precautions (5.6)]
- Hyperglycemia and Hyperosmolar Hyperglycemic State [see Warnings and Precautions (5.7)]
- Hypercalcemia [see Warnings and Precautions (5.8)]
- Fluid Overload [see Warnings and Precautions (5.9)]
- Acid/Base Imbalances [see Warnings and Precautions (5.10)]

The following adverse reactions have been identified during postapproval use of Lactated Ringer’s products. Because these reactions are reported voluntarily from a population of uncertain size, it is not always possible to reliably estimate their frequency or establish a causal relationship to drug exposure:

General Disorders and Administration Site Conditions:
  Phlebitis, extravasation, infusion site inflammation, infusion site swelling, infusion site rash, infusion site pruritus, infusion site erythema, infusion site pain, infusion site burning, and infusion site hypoaesthesia.
Hypersensitivity Reactions and Infusion Reactions:
  Angioedema, chest pain/discomfort, bradycardia or tachycardia, hypotension, respiratory distress, bronchospasm, dyspnea, cough, urticaria, rash, pruritus, erythema, flushing, throat irritation, paresthesia, oral hypoesthesia, dysgeusia, nausea, anxiety, pyrexia, and headache, laryngeal edema, sneezing, injection site infection.
Metabolism and Nutrition Disorders:
  Hyperkalemia, hyponatremia, and hypervolemia.
Nervous System Disorders:
  Hyponatremic encephalopathy.

7 DRUG INTERACTIONS

7.1 Drugs that Affect Electrolyte and/or Fluid Balance

Hyperkalemia
Administration of Potassium Chloride in Lactated Ringer’s and Dextrose (5%) Injection to patients concomitantly treated or recently treated with drugs that are associated with hyperkalemia increases the risk of severe and potentially fatal hyperkalemia, especially in the presence of other hyperkalemia risk factors. Avoid use of Potassium Chloride in Lactated Ringer’s and Dextrose (5%) Injection in patients receiving drugs that are associated with hyperkalemia (e.g., potassium-sparing diuretics, ACE inhibitors, angiotensin II receptor antagonists, or calcineurin inhibitors). If concomitant use cannot be avoided, closely monitor serum potassium concentrations during concomitant use [see Warnings and Precautions (5.4)].

Hyponatremia
Administration of Potassium Chloride in Lactated Ringer’s and Dextrose (5%) Injection to patients treated concomitantly with drugs associated with hyponatremia may increase the risk of developing hyponatremia. These drugs include diuretics and those that cause SIADH (e.g., arginine vasopressin analogs, certain antiepileptic, psychotropic, or cytotoxic drugs). Avoid use of Potassium Chloride in Lactated Ringer’s and Dextrose (5%) Injection in patients receiving such drugs. If use cannot be avoided, closely monitor serum sodium concentrations during concomitant use [see Warnings and Precautions (5.5)].

Hypercalcemia
Avoid the use of Potassium Chloride in Lactated Ringer’s and Dextrose (5%) Injection in patients treated with thiazide diuretics or vitamin D because these drugs can increase the risk of hypercalcemia. If use cannot be avoided, closely monitor serum calcium concentrations during concomitant use [see Warnings and Precautions (5.8)].

Hypernatremia and Fluid Retention
Administration of Potassium Chloride in Lactated Ringer’s and Dextrose (5%) Injection to patients treated concomitantly with drugs associated with sodium and fluid retention (e.g., corticosteroids or corticotropin) may increase the risk of hypernatremia and volume overload. Avoid use of Potassium Chloride in Lactated Ringer’s and Dextrose (5%) Injection in patients receiving such drugs. If use cannot be avoided, closely monitor serum electrolytes, fluid balance, and acid-base balance during concomitant use.

7.2 Lithium

Renal sodium and lithium clearance may be increased during concomitant use of Potassium Chloride in Lactated Ringer’s and Dextrose (5%) Injection and lithium and may result in decreased lithium concentrations. Avoid use of Potassium Chloride in Lactated Ringer’s and Dextrose (5%) Injection in patients receiving lithium. If use cannot be avoided, increase the frequency of monitoring of serum lithium concentrations during concomitant use.

7.3 Digoxin

Administration of calcium via use of Potassium Chloride in Lactated Ringer’s and Dextrose (5%) Injection may increase digoxin’s effects and lead to digoxin toxicity including serious or fatal cardiac arrhythmias. In digoxin-treated patients, consider reducing the volume and/or rate of Potassium Chloride in Lactated Ringer’s and Dextrose (5%) Injection administration.

7.4 Drugs with pH-Dependent Renal Elimination

Due to the alkalinizing action of lactate (formation of bicarbonate), Potassium Chloride in Lactated Ringer’s and Dextrose (5%) Injection may interfere with the elimination of drugs with pH-dependent renal elimination. Renal clearance of alkaline drugs may be decreased. In contrast, renal clearance of acidic drugs may be increased.

7.5 Interference of Potassium Chloride in Lactated Ringer’s and Dextrose (5%) Injection with Interpretation of Serum Lactate Levels in Patients with Severe Metabolic Acidosis

Because administration of Potassium Chloride in Lactated Ringer’s and Dextrose (5%) Injection may interfere with the interpretation of serum lactate levels in patients with severe metabolic acidosis, including lactic acidosis, assessment of the patient’s clinical status should not solely rely on the measurement of serum lactate.

8 USE IN SPECIFIC POPULATIONS

8.1 Pregnancy

Risk Summary
Potassium Chloride in Lactated Ringer’s and Dextrose (5%) Injection as a source of water and electrolytes has been used for decades during labor and delivery. Appropriate administration of Potassium Chloride in Lactated Ringer’s and Dextrose (5%) Injection is not expected to cause major birth defects, miscarriage, or adverse maternal or fetal outcomes. Animal reproduction studies have not been conducted with this drug.

The background risk of major birth defects and miscarriage for the indicated population is unknown. All pregnancies have a background risk of birth defect, loss, or other adverse outcomes. In the U.S. general population, the estimated background risk of major birth defects and miscarriage in clinically recognized pregnancies is 2 to 4% and 15 to 20%, respectively.

8.2 Lactation

Risk Summary
Lactated Ringer’s as a source of water and electrolytes and Dextrose (5%) Injection have been used for decades and is not expected to cause harm to a breastfed infant. There are no data on the presence of Lactated Ringer’s and Dextrose (5%) Injection in human milk, the effects on the breastfed infant, or the effects on milk production. Potassium is present in human breast milk. There are no data on the effects of Potassium Chloride in Lactated Ringer’s and Dextrose (5%) Injection on a breastfed infant or the effects on milk production. The developmental and health benefits of breastfeeding should be considered along with the mother’s clinical need for Potassium Chloride in Lactated Ringer’s and Dextrose (5%) Injection and any potential adverse effects on the breastfed infant from Potassium Chloride in Lactated Ringer’s and Dextrose (5%) Injection or from the underlying maternal condition.

8.4 Pediatric Use

Potassium Chloride in Lactated Ringer’s and Dextrose (5%) Injection is contraindicated in neonates (28 days of age or younger) who are receiving ceftriaxone due to reported deaths that occurred when neonates received ceftriaxone and intravenous calcium-containing solutions concomitantly [see Warnings and Precautions (5.1)].

The safety and effectiveness of Lactated Ringer’s Injection for use as a source of water, electrolytes, and calories or as an alkalinizing agent have been established in pediatric patients of all ages, including neonates.

The safety profile of Potassium Chloride in Dextrose Injection in pediatric patients is similar to adults.

Closely monitor plasma electrolyte concentrations in young pediatric patients with immature kidney function who may have decreased ability to maintain fluid and electrolyte balance [see Warnings and Precautions (5.4, 5.5, 5.8, 5.9)]. Administration of a lactate-containing intravenous solution, including Potassium Chloride in Lactated Ringer’s and Dextrose (5%) Injection to pediatric patients should account for liver and kidney maturation (the kidney function affects the biotransformation and renal excretion of lactate) [see Warnings and Precautions (5.9)]. Pediatric patients are at increased risk for developing hyponatremic encephalopathy [see Warnings and Precautions (5.5)].

Neonates, especially preterm neonates with low birth weight, are at increased risk of developing hypo- or hyperglycemia and therefore need close monitoring during treatment with intravenous glucose solutions including Potassium Chloride in Lactated Ringer’s and Dextrose (5%) Injection to ensure adequate glycemic control to avoid potential long-term adverse reactions [see Warnings and Precautions (5.6, 5.7)]. In very low birth weight neonates, excessive or rapid administration of Potassium Chloride in Lactated Ringer’s and Dextrose (5%) Injection may result in increased serum osmolarity and risk of intracranial hemorrhage.

8.5 Geriatric Use

Geriatric patients treated with Potassium Chloride in Lactated Ringer’s and Dextrose (5%) Injection are at increased risk of developing electrolyte imbalances. Potassium Chloride in Lactated Ringer’s and Dextrose (5%) Injection is substantially excreted by the kidney, and the risk of adverse reactions to Potassium Chloride in Lactated Ringer’s and Dextrose (5%) Injection may be greater in patients with renal impairment than in patients with normal renal function. Because geriatric patients are more likely to have decreased renal function, consider monitoring renal function in geriatric patients and consider starting the infusion at the low end of the dosing range.

8.6 Renal Impairment

Administration of Potassium Chloride in Lactated Ringer’s and Dextrose (5%) Injection to patients with or at risk of severe renal impairment, may result in hyperkalemia and/or fluid overload [see Warnings and Precautions (5.4, 5.7, 5.9)]. Avoid Potassium Chloride in Lactated Ringer’s and Dextrose (5%) Injection in patients with severe renal impairment. If use cannot be avoided in such patients, monitor for development of these adverse reactions.

8.7 Hepatic Impairment

In patients with severe hepatic impairment, lactate metabolism may be impaired, and Potassium Chloride in Lactated Ringer’s and Dextrose (5%) Injection may not produce alkalinization. Closely monitor serum lactate levels and acid-base status in such patients.

10 OVERDOSAGE

Excessive administration of Potassium Chloride in Lactated Ringer’s and Dextrose (5%) Injection can cause:

- Hyperkalemia and hypernatremia, especially in patients with severe renal impairment.
- Fluid overload (which can lead to pulmonary and/or peripheral edema).
- Hyperglycemia, hyperosmolarity, and osmotic diuresis, dehydration, and electrolyte loss.
- Metabolic alkalosis with or without hypokalemia.
- Loss of bicarbonate with an acidifying effect.
- Hypercalcemia.

Overdose interventions include Potassium Chloride in Lactated Ringer’s and Dextrose (5%) Injection discontinuation, treatment of electrolyte imbalances, treatment of hyperglycemia, and close monitoring of fluid balance, electrolyte concentrations, and acid-base balance [see Warnings and Precautions (5.4, 5.5, 5.6, 5.7, 5.9, 5.10)]

11 DESCRIPTION

Potassium Chloride in Lactated Ringer’s and Dextrose (5%) Injection, USP is a sterile, nonpyrogenic solution for fluid and electrolyte replenishment and caloric supply in a single dose container for intravenous administration. It contains no antimicrobial agents. Composition, osmolarity, pH, ionic concentration and caloric content are shown in Table 1. Dextrose is derived from corn.

Table 1
Potassium Chloride in Lactated Ringer’s and Dextrose (5%) Injection, USP | Size (mL) | Composition (g/L) |  |  |  |  | [Normal physiologic osmolarity range is approximately 280 to 310 mOsmol/L.] Osmolarity (mOsmol/L) (calc) | pH | Ionic Concentration (mEq/L) |  |  |  |  | Caloric Content (kcal/L)
Potassium Chloride in Lactated Ringer’s and Dextrose (5%) Injection, USP | Size (mL) | Dextrose, USP | Sodium Chloride, USP | Sodium Lactate | Potassium Chloride, USP | Calcium Chloride, USP | [Normal physiologic osmolarity range is approximately 280 to 310 mOsmol/L.] Osmolarity (mOsmol/L) (calc) | pH | Sodium | Potassium | Calcium | Chloride | Lactate | Caloric Content (kcal/L)
20 mEq Potassium added | 1000 | 50 | 6 | 3.1 | 1.79 | 0.2 | 565 | 5.0; (3.5 to; 6.5) | 130 | 24 | 3 | 129 | 28 | 170

The chemical name, structural formula, and molecular weight of the active ingredients are shown in Table 2.

Table 2
Chemical Name | Structural Formula | Molecular Weight
Sodium Chloride, USP |  | 58.44
Sodium Lactate |  | 112.06
Potassium Chloride, USP |  | 74.55
Calcium Chloride, USP |  | 147.02
Dextrose, USP |  | 198.17

The VIAFLEX plastic container is fabricated from polyvinyl chloride (PL 146 Plastic). Small amounts of its chemical components (e.g., di-2-ethylhexyl phthalate [DEHP]) may leach out within the expiration period. Animal tests, USP biological tests for plastic containers, and tissue culture toxicity studies have demonstrated that the container meets safety requirements. The container is overwrapped to provide protection from the physical environment and an additional moisture barrier.

12 CLINICAL PHARMACOLOGY

12.1 Mechanism of Action

Potassium Chloride in Lactated Ringer’s and Dextrose (5%) Injection is a source of water, electrolytes, and calories, and produces an alkalinizing effect.

- Sodium, the major cation of the extracellular fluid, functions primarily in the control of water distribution, fluid balance, and osmotic pressure of body fluids. Sodium is also associated with chloride and bicarbonate in the regulation of the acid-base equilibrium of body fluid.
- Potassium, the principal cation of intracellular fluid, participates in carbohydrate utilization and protein synthesis and is critical in the regulation of nerve conduction and muscle contraction, particularly in the heart.
- Chloride, the major extracellular anion, closely follows the metabolism of sodium, and changes in the acid-base balance of the body are reflected by changes in the chloride concentration.
- Calcium, an important cation, provides the framework of bones and teeth in the form of calcium phosphate and calcium carbonate. In the ionized form, calcium is essential for the functional mechanism of the clotting of blood, normal cardiac function, and regulation of neuromuscular irritability.
- Sodium lactate provides sodium and lactate ions. The lactate anion is in equilibrium with pyruvate and has an alkalinizing effect resulting from simultaneous removal by the liver of lactate and hydrogen ions. The sodium ion combines with bicarbonate ion produced from carbon dioxide of the body and thus retains bicarbonate to combat metabolic acidosis (bicarbonate deficiency).
- Dextrose provides a source of calories. Dextrose may decrease losses of body protein and nitrogen, promotes glycogen deposition and decreases or prevents ketosis if sufficient doses are provided.

12.2 Pharmacodynamics

The exposure-response relationship and time course of pharmacodynamic response for the safety and effectiveness of Potassium Chloride in Lactated Ringer’s and Dextrose (5%) Injection have not been fully characterized.

12.3 Pharmacokinetics

Elimination
Metabolism/Excretion

Potassium: Normally about 80 to 90% of the potassium intake is excreted in the urine; the remainder is excreted in feces and to a smaller extent, in perspiration.

Sodium and Chloride: The distribution and excretion of sodium (Na+) and chloride (Cl−) are largely under the control of the kidney which maintains a balance between intake and output.

Lactate: In the liver, lactate is metabolized to carbon dioxide and water by oxidative metabolism and consumption of hydrogen cations.

Dextrose: Dextrose injected parenterally undergoes oxidation to carbon dioxide and water.

13 NONCLINICAL TOXICOLOGY

13.1 Carcinogenesis, Mutagenesis, Impairment of Fertility

Carcinogenicity, genetic toxicology, and animal fertility studies have not been conducted with Potassium Chloride in Lactated Ringer’s and Dextrose (5%) Injection.

16 HOW SUPPLIED/STORAGE AND HANDLING

How Supplied
Potassium Chloride in Lactated Ringer’s and Dextrose (5%) Injection, USP is supplied as a clear solution in single-dose VIAFLEX plastic containers as follows:

Code | Size (mL) | NDC | Product Name
2B2224 | 1000 | 0338-0811-04 | 20 mEq/L Potassium Chloride in Lactated Ringer’s and 5% Dextrose Injection, USP

Storage and Handling
Store at room temperature (recommended 25°C/77°F).

Brief exposure up to 40°C (104°F) does not adversely affect the product. Exposure to heat should be minimized. Avoid excessive heat.

Baxter Healthcare Corporation
Deerfield, IL 60015 USA

Baxter, PL 146 and Viaflex are trademarks of Baxter International Inc. or its subsidiaries.

07-19-00-9427

PACKAGE/LABEL PRINCIPAL DISPLAY PANEL

Container Label

LOT

EXP

2B2224
NDC 0338-0811-04
DIN 00786314

20 mEq

Potassium Chloride

(20 mEq/L) Potassium Chloride in
Lactated Ringer's and 5% Dextrose
Injection USP

1000 mL

EACH 100 mL CONTAINS 5 g DEXTROSE HYDROUS USP 600 mg
SODIUM CHLORIDE USP 310 mg SODIUM LACTATE 179 mg
POTASSIUM CHLORIDE USP 20 mg CALCIUM CHLORIDE USP pH
5.0 (3.5 TO 6.5) mEq/L SODIUM 130 POTASSIUM 24
CALCIUM 3 CHLORIDE 129 LACTATE 28 HYPERTONIC
OSMOLARITY 565 mOsmol/L (CALC) STERILE NONPYROGENIC
SINGLE DOSE CONTAINER NOT FOR USE IN THE TREATMENT OF
LACTIC ACIDOSIS ADDITIVES MAY BE INCOMPATIBLE CONSULT WITH
PHARMACIST IF AVAILABLE WHEN INTRODUCING ADDITIVES USE
ASEPTIC TECHNIQUE MIX THOROUGHLY DO NOT STORE DOSAGE
INTRAVENOUSLY AS DIRECTED BY A PHYSICIAN SEE DIRECTIONS
CAUTIONS SQUEEZE AND INSPECT INNER BAG WHICH MAINTAINS
PRODUCT STERILITY DISCARD IF LEAKS ARE FOUND MUST NOT BE
USED IN SERIES CONNECTIONS DO NOT ADMINISTER
SIMULTANEOUSLY WITH BLOOD DO NOT USE UNLESS SOLUTION IS
CLEAR Rx ONLY STORE UNIT IN MOISTURE BARRIER OVERWRAP AT
ROOM TEMPERATURE (25°C/77°F) UNTIL READY TO USE AVOID
EXCESSIVE HEAT SEE INSERT

VIAFLEX PLUS CONTAINER

PL 146 PLASTIC

BAXTER VIAFLEX AND PL 146 ARE TRADEMARKS OF
BAXTER INTERNATIONAL INC

FOR PRODUCT INFORMATION 1-800-933-0303

Baxter
BAXTER HEALTHCARE CORPORATION
DEERFIELD IL 60015 USA

MADE IN USA

DISTRIBUTED IN CANADA BY
BAXTER CORPORATION
TORONTO ONTARIO CANADA